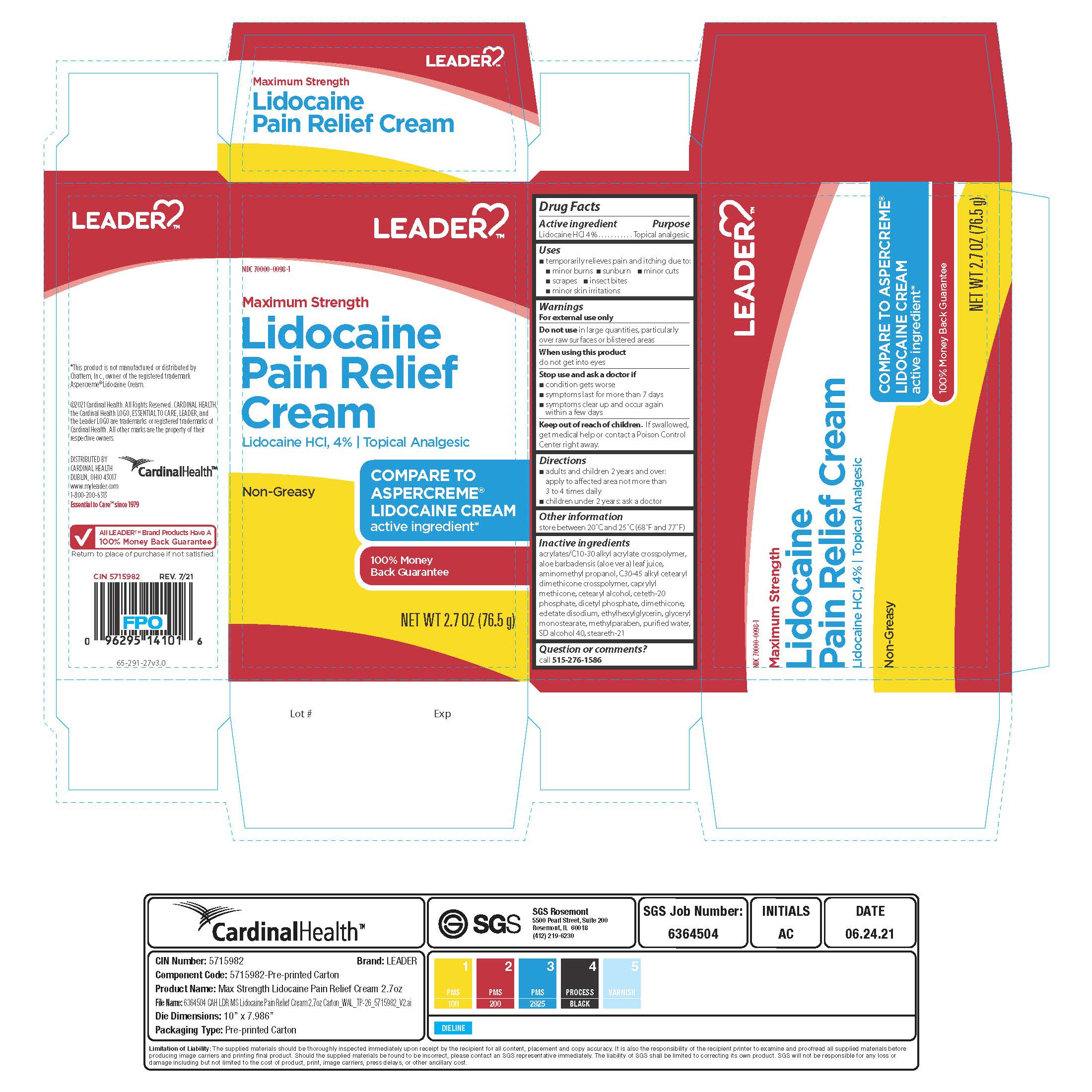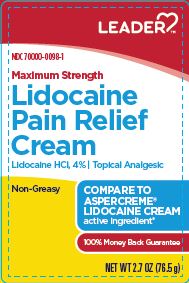 DRUG LABEL: Leader
NDC: 70000-0098 | Form: CREAM
Manufacturer: Cardinal Health
Category: otc | Type: HUMAN OTC DRUG LABEL
Date: 20241219

ACTIVE INGREDIENTS: LIDOCAINE HYDROCHLORIDE 4 g/100 g
INACTIVE INGREDIENTS: WATER; EDETATE DISODIUM; DIHEXADECYL PHOSPHATE; DIMETHICONE 350; ALOE VERA LEAF; CETOSTEARYL ALCOHOL; METHYLPARABEN; ETHYLHEXYLGLYCERIN; AMINOMETHYLPROPANOL; GLYCERYL STEARATE SE; CETETH-20 PHOSPHATE; STEARETH-21; CAPRYLYL TRISILOXANE; ALCOHOL

Leader Lidocaine HCL 4% Cream

Active ingredient

Lidocaine HCl 4%

Purpose

Topical analgesic

Uses

temporarily relieves pain and itching due to:

- minor burns
- sunburn
- minor cuts
- scrapes
- insect bites
- minor skin irritations

Warnings

For external use only

Do not use in large quantities, particularly over raw surfaces or blistered areas

When using this product do not get into eyes

Stop use and ask a doctor if

- condition gets worse
- symptoms last for more than 7 days
- symptoms clear up and occur again within a few days

Keep out of reach of children. If swallowed, get medical help or contact a Poison Control Center right away.

Directions

- adults and children 2 years and over: apply to affected area not more than 3 to 4 times daily
- children under 2 years: ask a doctor

Other information

store between 20 °C and 25 °C (68 °F and 77 °F)

Inactive ingredients

acrylates/C10-30 alkyl acrylate crosspolymer, aloe barbadensis (aloe vera) leaf juice, aminomethyl propanol,
C30-45 alkyl cetearyl dimethicone crosspolymer, caprylyl methicone, cetearyl alcohol, ceteth-20 phosphate, dicetyl phosphate, dimethicone, edetate disodium, ethylhexylglycerin, glyceryl monostearate, methylparaben, purified water, SD alcohol 40, steareth-21

Principal display panel

Leader

NDC 70000-0098-1

Maximum Strength

Lidocaine

Pain Relief

Cream

Lidocaine HCl 4% Topical Analgesic

Non Greasy

Compare to aspercreme lidocaine cream

active ingredient

100% Money Back Guarantee

Net wt 2.7 oz (76.5g)